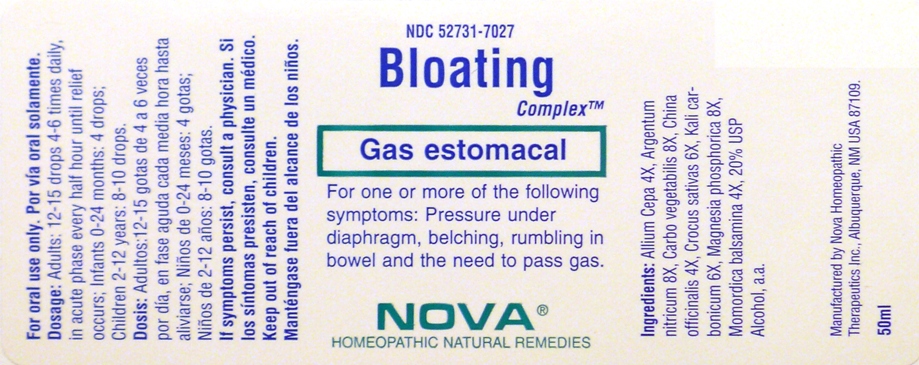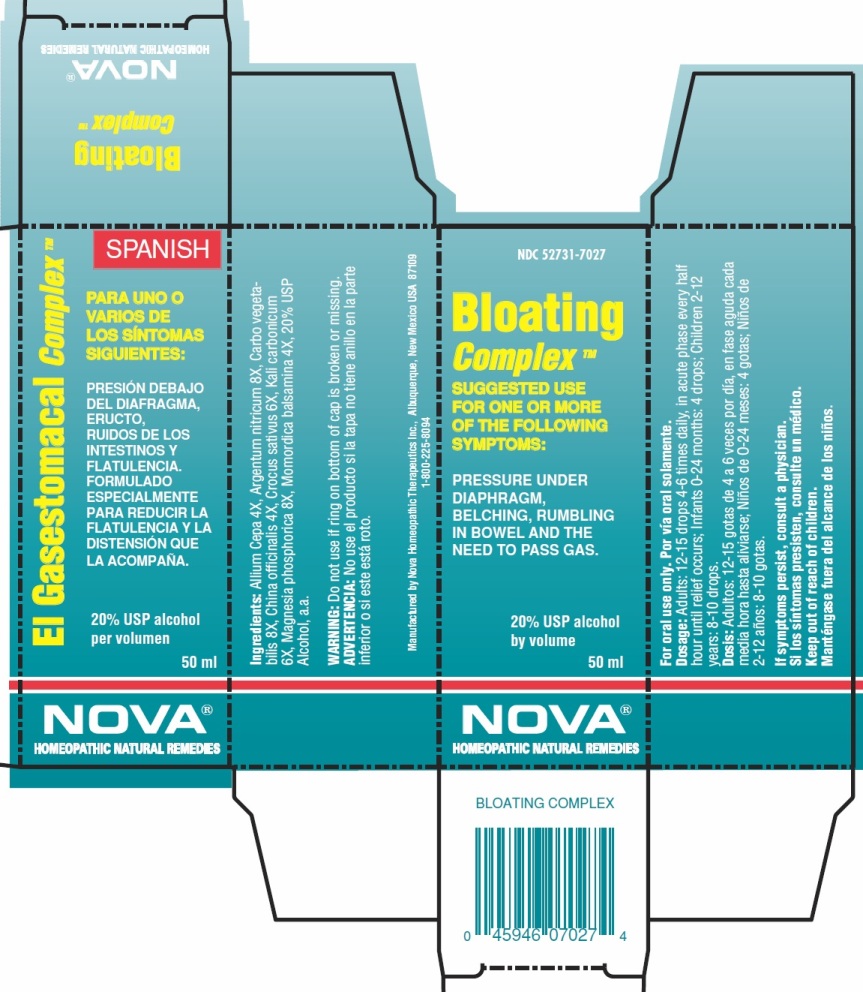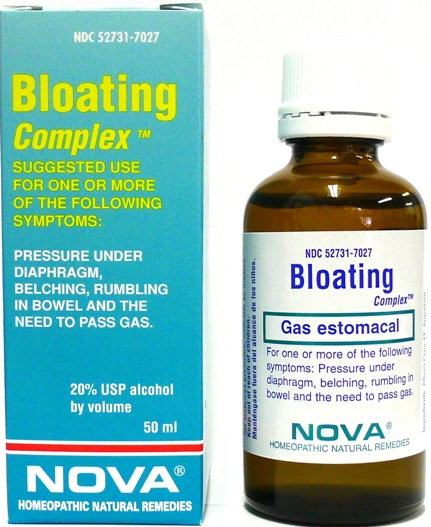 DRUG LABEL: Bloating Complex
NDC: 52731-7027 | Form: LIQUID
Manufacturer: Nova Homeopathic Therapeutics, Inc.
Category: homeopathic | Type: HUMAN OTC DRUG LABEL
Date: 20110601

ACTIVE INGREDIENTS: ONION 4 [hp_X]/1 mL; SILVER NITRATE 8 [hp_X]/1 mL; ACTIVATED CHARCOAL 8 [hp_X]/1 mL; CINCHONA PUBESCENS BARK 4 [hp_X]/1 mL; SAFFRON 6 [hp_X]/1 mL; POTASSIUM CARBONATE 6 [hp_X]/1 mL; MAGNESIUM PHOSPHATE, DIBASIC TRIHYDRATE 8 [hp_X]/1 mL; MOMORDICA BALSAMINA IMMATURE FRUIT 4 [hp_X]/1 mL
INACTIVE INGREDIENTS: ALCOHOL .2 mL/1 mL

Bloating Complex

Purpose:

Suggested use for one or more of the following symptoms:

Pressure under diaphragm, belching, rumbling in bowel and the need to pass gas.

Usage and Dosage:

For oral use only.

DOSAGE AND ADMINISTRATION

Adults:
In Acute Phase:
12-15 drops, every half hour until relief occurs
When Relief Occurs:
12-15 drops, 4-6 times per day
Children 2-12 years:
8-10 drops, 4-6 times per day
Infants 0-24 months:
4 drops, 4-6 times per day

Warnings:

Keep out of reach of children.

WARNINGS

If symptoms persist, consult a physician.

Do not use if ring on bottom of cap is broken or missing.

Active Ingredients:

Allium Cepa 4X, Argentum nitricum 8X, Carbo vegetabilis
8X, China officinalis 4X, Crocus sativus 6X, Kali carbonicum
6X, Magnesia phosphorica 8X, Momordica balsamina 4X

Inactive Ingredients:

Alcohol, 20% USP

QUESTIONS

Manufactured by Nova Homeopathic Therapeutics Inc., Albuquerque, New Mexico USA 87109
1-800-225-8094

PACKAGE LABEL

Bloating Complex Product

Bloating Complex Bottle Label

Bloating Complex Box